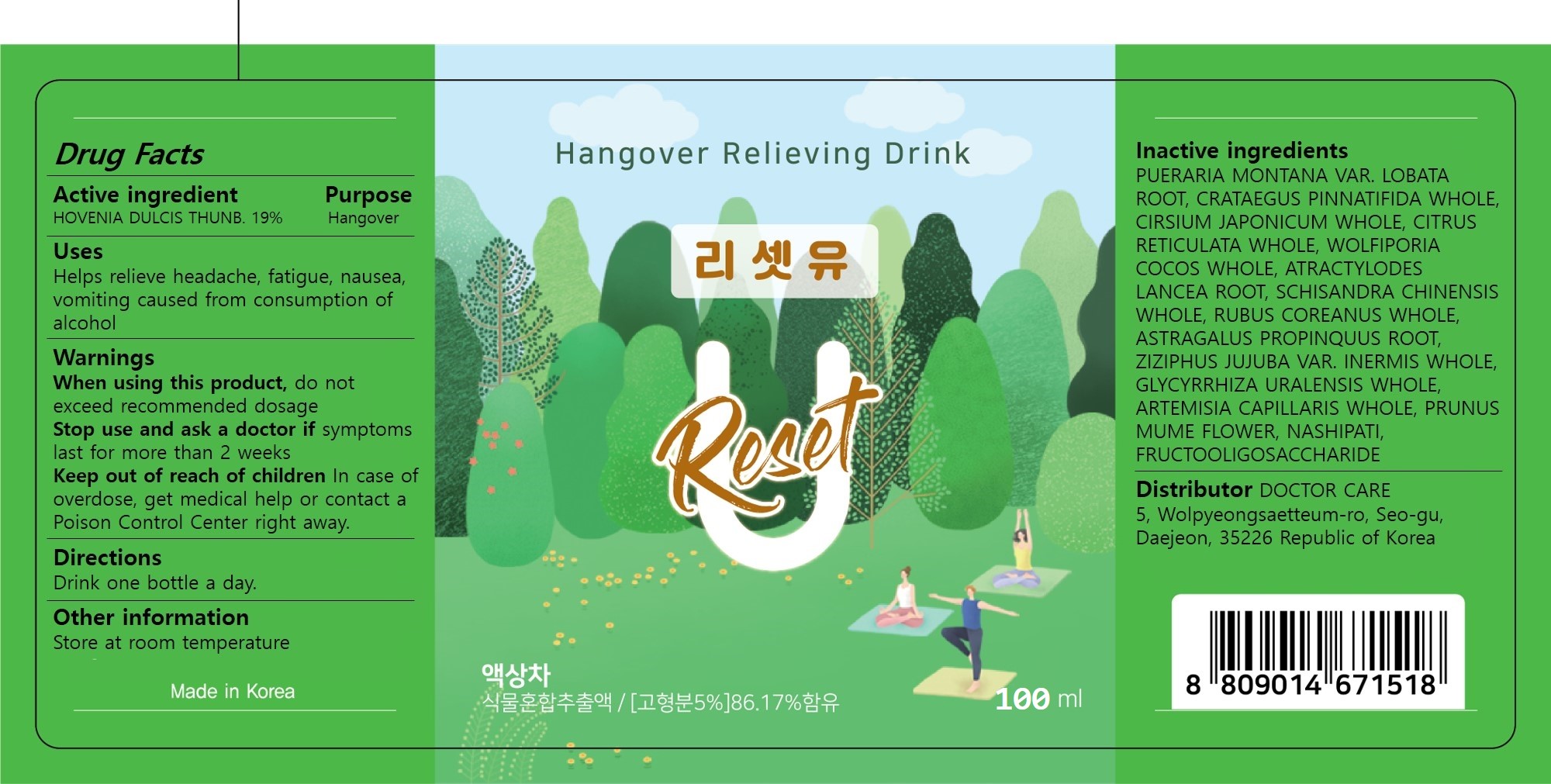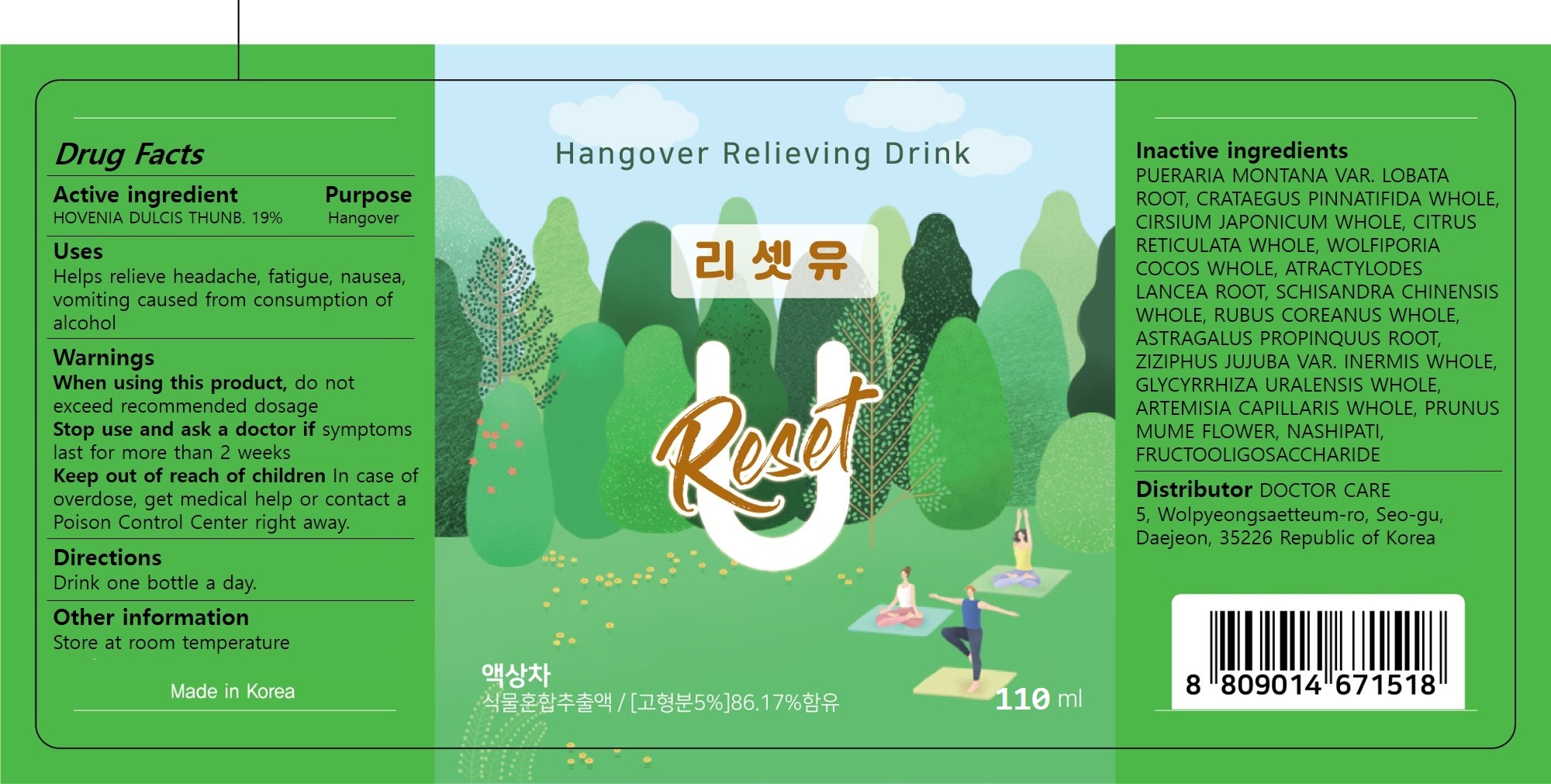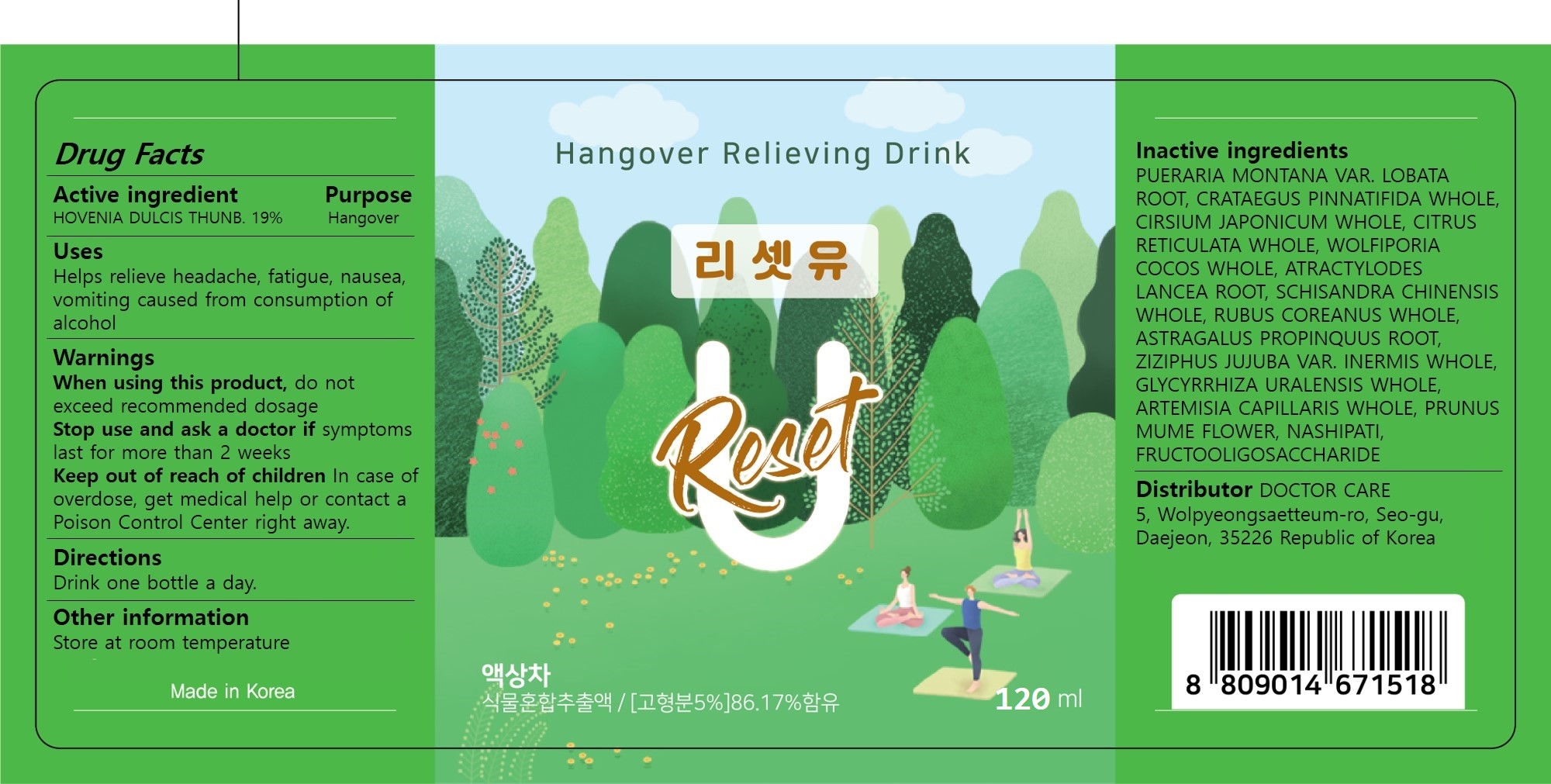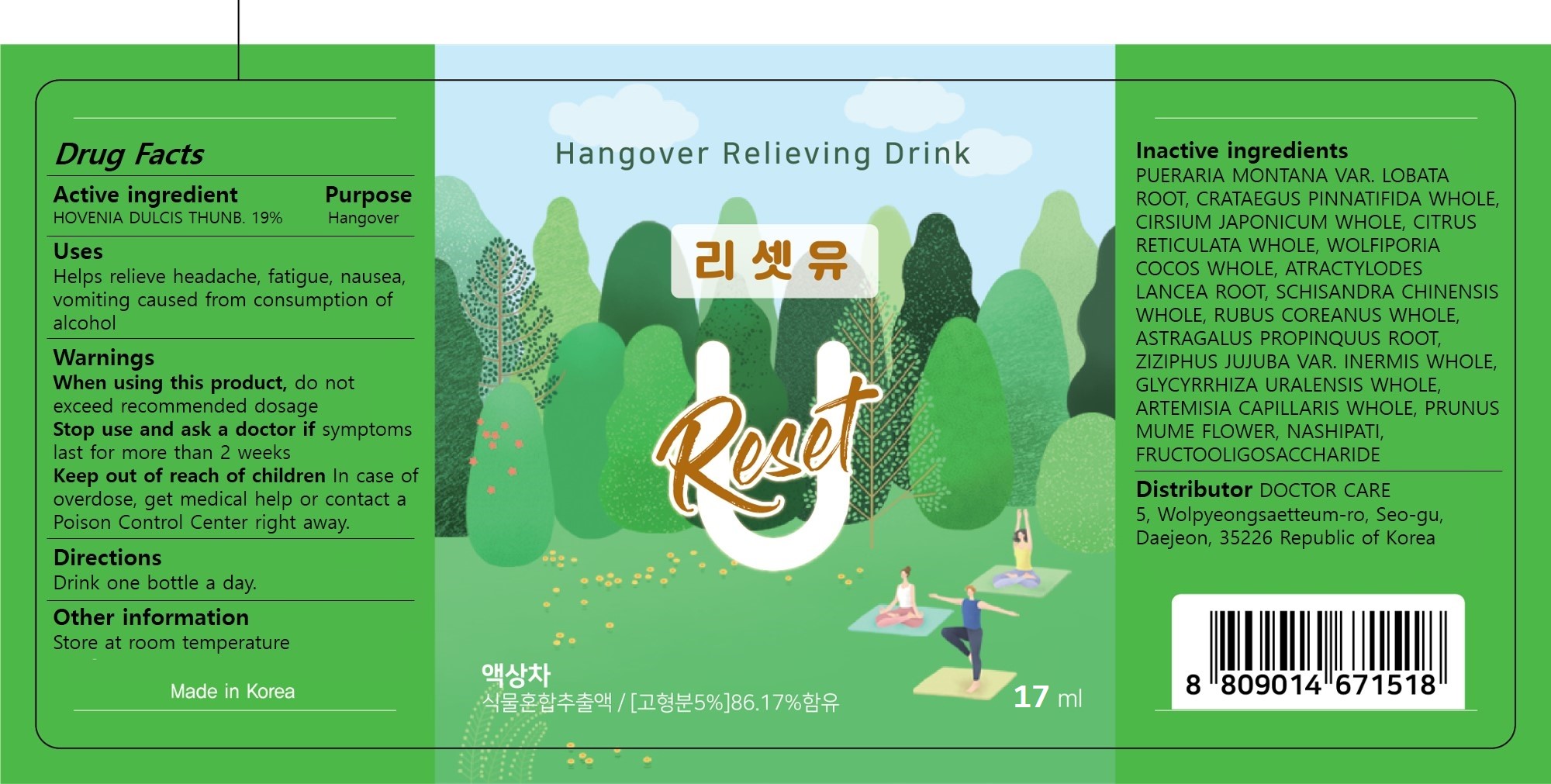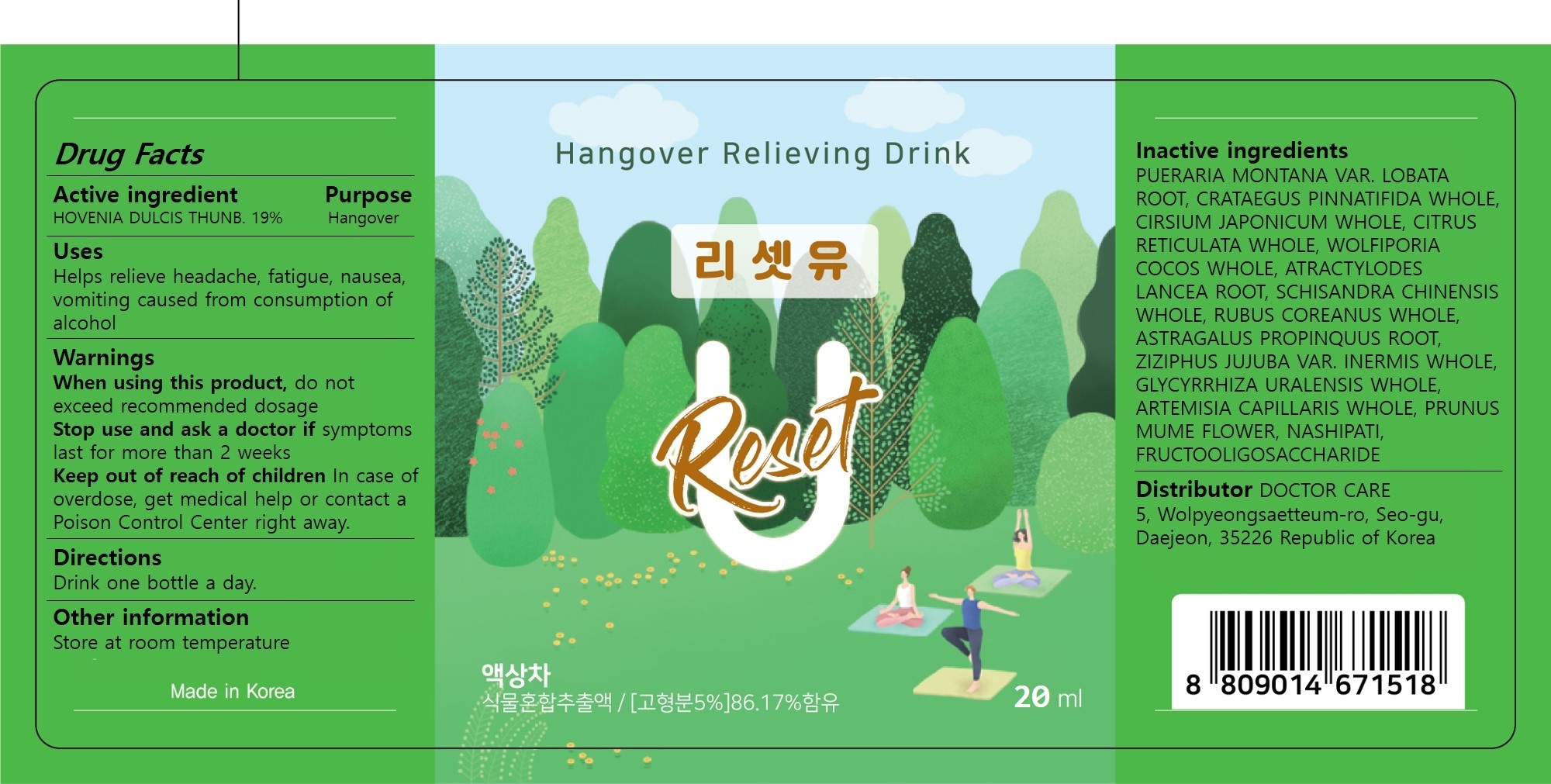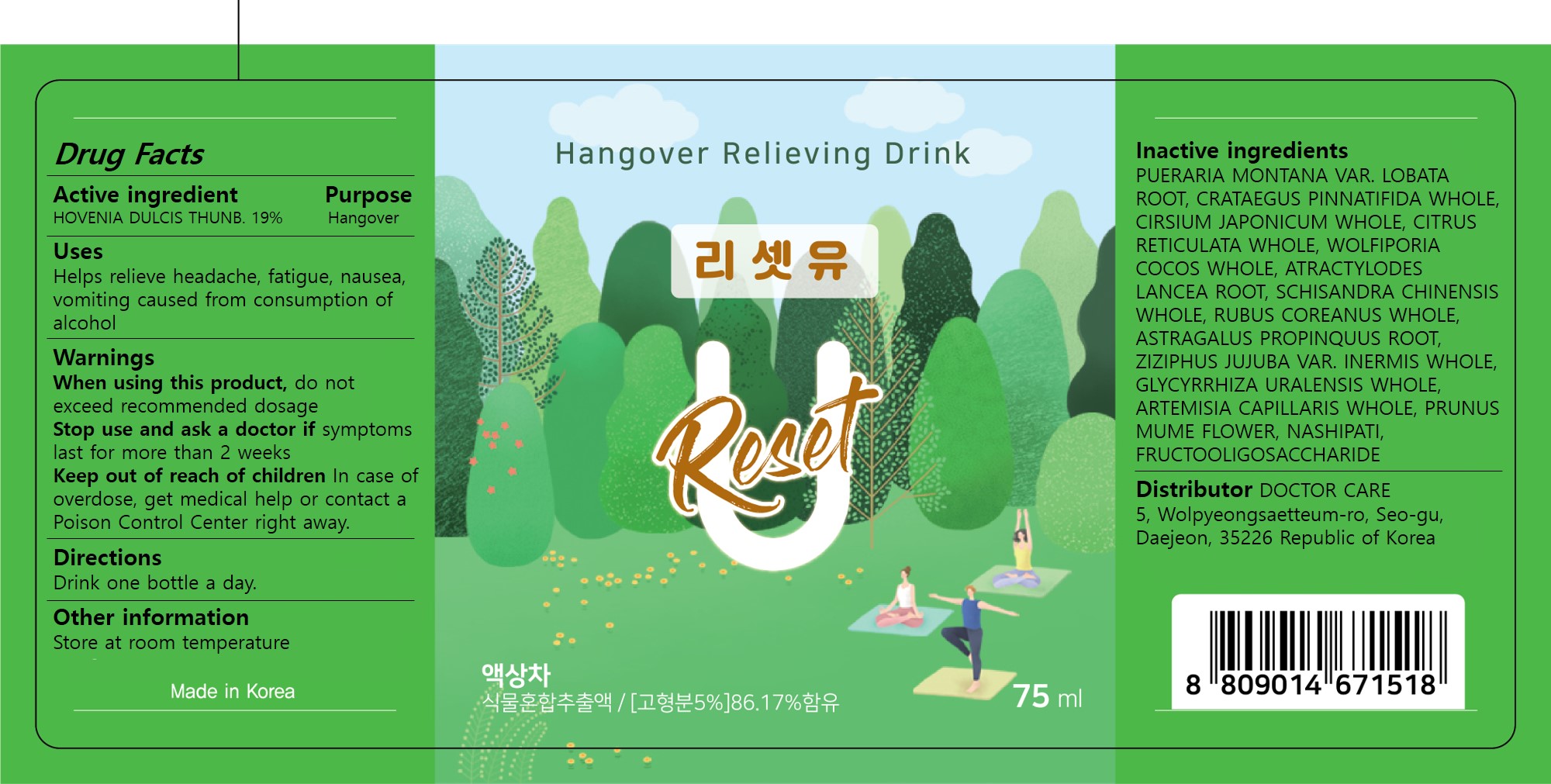 DRUG LABEL: Reset U
NDC: 82229-001 | Form: LIQUID
Manufacturer: DOCTOR CARE
Category: otc | Type: HUMAN OTC DRUG LABEL
Date: 20231117

ACTIVE INGREDIENTS: HOVENIA DULCIS WHOLE 19 g/100 mL
INACTIVE INGREDIENTS: SCHISANDRA CHINENSIS WHOLE; ARTEMISIA CAPILLARIS WHOLE; NASHIPATI; PUERARIA MONTANA VAR. LOBATA ROOT; CRATAEGUS PINNATIFIDA WHOLE; CITRUS RETICULATA WHOLE; WOLFIPORIA COCOS WHOLE; ASTRAGALUS PROPINQUUS ROOT; PRUNUS MUME FLOWER; ATRACTYLODES LANCEA ROOT; CIRSIUM JAPONICUM; RUBUS COREANUS WHOLE; ZIZIPHUS JUJUBA VAR. INERMIS WHOLE; GLYCYRRHIZA URALENSIS WHOLE

82229-001 Reset U

Active ingredient

HOVENIA DULCIS THUNB. 19%

Purpose

Hangover

Uses

Helps relieve headache, fatigue, nausea, vomiting caused from consumption of alcohol

When using this product,

do not exceed recommended dosage

Stop use and ask a doctor if

symptoms last for more than 2 weeks

Keep out of reach of children

In case of overdose, get medical help or contact a Poison Control Center right away.

Directions

Drink one bottle a day.

Other information

Store at room temperature

Inactive ingredients

PUERARIA MONTANA VAR. LOBATA ROOT, CRATAEGUS PINNATIFIDA WHOLE, CIRSIUM JAPONICUM WHOLE, CITRUS RETICULATA WHOLE, WOLFIPORIA COCOS WHOLE, ATRACTYLODES LANCEA ROOT, SCHISANDRA CHINENSIS WHOLE, RUBUS COREANUS WHOLE, ASTRAGALUS PROPINQUUS ROOT, ZIZIPHUS JUJUBA VAR. INERMIS WHOLE, GLYCYRRHIZA URALENSIS WHOLE, ARTEMISIA CAPILLARIS WHOLE, PRUNUS MUME FLOWER, NASHIPATI, FRUCTOOLIGOSACCHARIDE